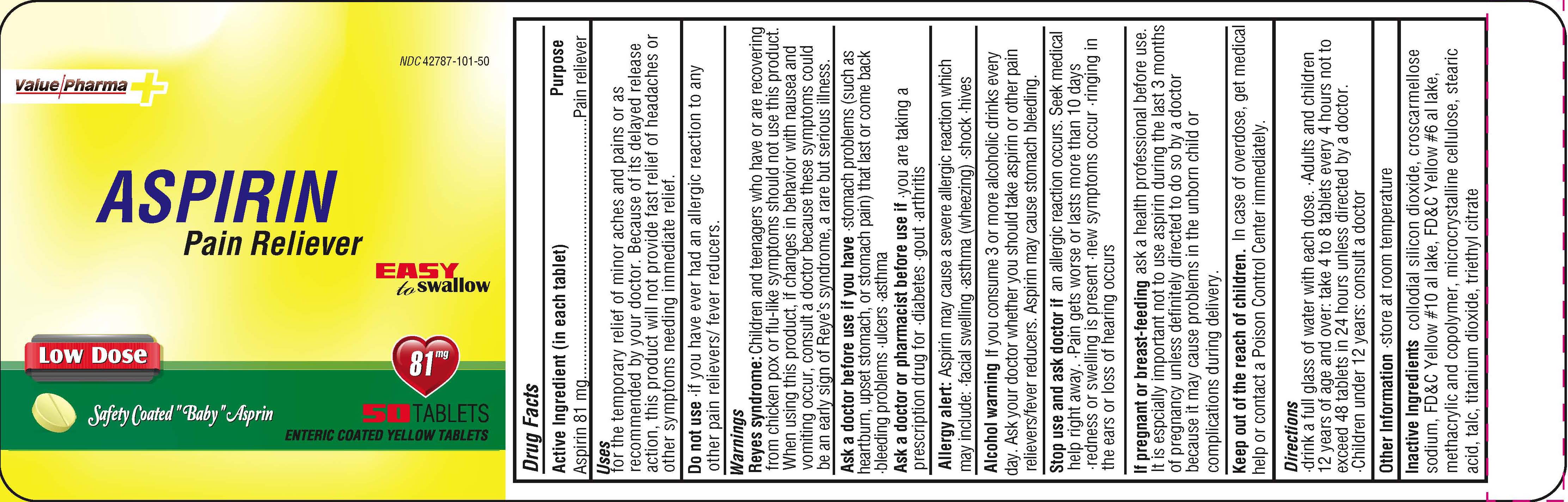 DRUG LABEL: Value Pharma

NDC: 42787-101 | Form: TABLET
Manufacturer: Ajes Pharmaceuticals,LLC
Category: otc | Type: HUMAN OTC DRUG LABEL
Date: 20181220

ACTIVE INGREDIENTS: ASPIRIN 81 mg/81 mg
INACTIVE INGREDIENTS: SILICON DIOXIDE; CROSCARMELLOSE SODIUM; CELLULOSE, MICROCRYSTALLINE; METHACRYLIC ACID - ETHYL ACRYLATE COPOLYMER (1:1) TYPE A; STEARIC ACID; TALC; TITANIUM DIOXIDE; TRIETHYL CITRATE

DRUG FACTS

ACTIVE INGREDIENT

ASPIRIN

Purpose

Pain Reliever

Inactive Ingredients

KEEP OUT OF REACH OF CHILDREN

In case of over dose get medical help and contact a Poison Control Center immediately.

INDICATIONS AND USAGE

For temporary relief of minor aches and pains or as recommended by your Doctor. Because of this products delayed release action, this product will not provide fast relief of headaches or symptoms needing immediate relief.

Do not use if you have ever had an allergic reaction to any other pain relievers/fever reducers. Children or teenagers who are recovering from the Chicken Pox or flu like symptoms should not use this product. When using this product if changes in behavior occur with nausea and vomiting occur,consult a Doctor because this could be a sign of Reye's Syndrome, a rare
but serious illness.

DOSAGE AND ADMINISTRATION

Directions - drink a full glass of water with each dose. Adults and children 12 years of age and over: take 4 to 8 tablets every 4 hours not to exceed48 tablets in 24 hours unless directed by a doctor. Children under 12 years: consult a doctor